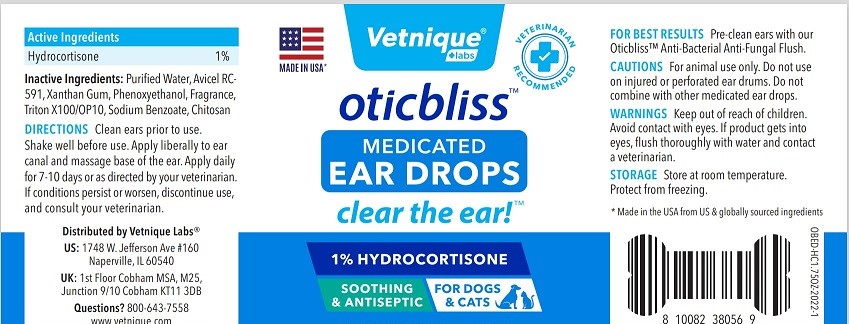 DRUG LABEL: OTICBLISS MEDICATED EAR DROPS
NDC: 80547-114 | Form: SOLUTION
Manufacturer: Vetnique Labs Llc
Category: animal | Type: OTC ANIMAL DRUG LABEL
Date: 20220621

ACTIVE INGREDIENTS: HYDROCORTISONE 1 g/100 mL
INACTIVE INGREDIENTS: WATER; MICROCRYSTALLINE CELLULOSE 101; CARBOXYMETHYLCELLULOSE SODIUM; XANTHAN GUM; PHENOXYETHANOL; OCTOXYNOL-9; SODIUM BENZOATE; CHITOSAN LOW MOLECULAR WEIGHT (20-200 MPA.S)

VETNIQUE - OTICBLISS MEDICATED EAR DROPS (80547-114)

Active Ingredients

HYDROCORTISONE 1%